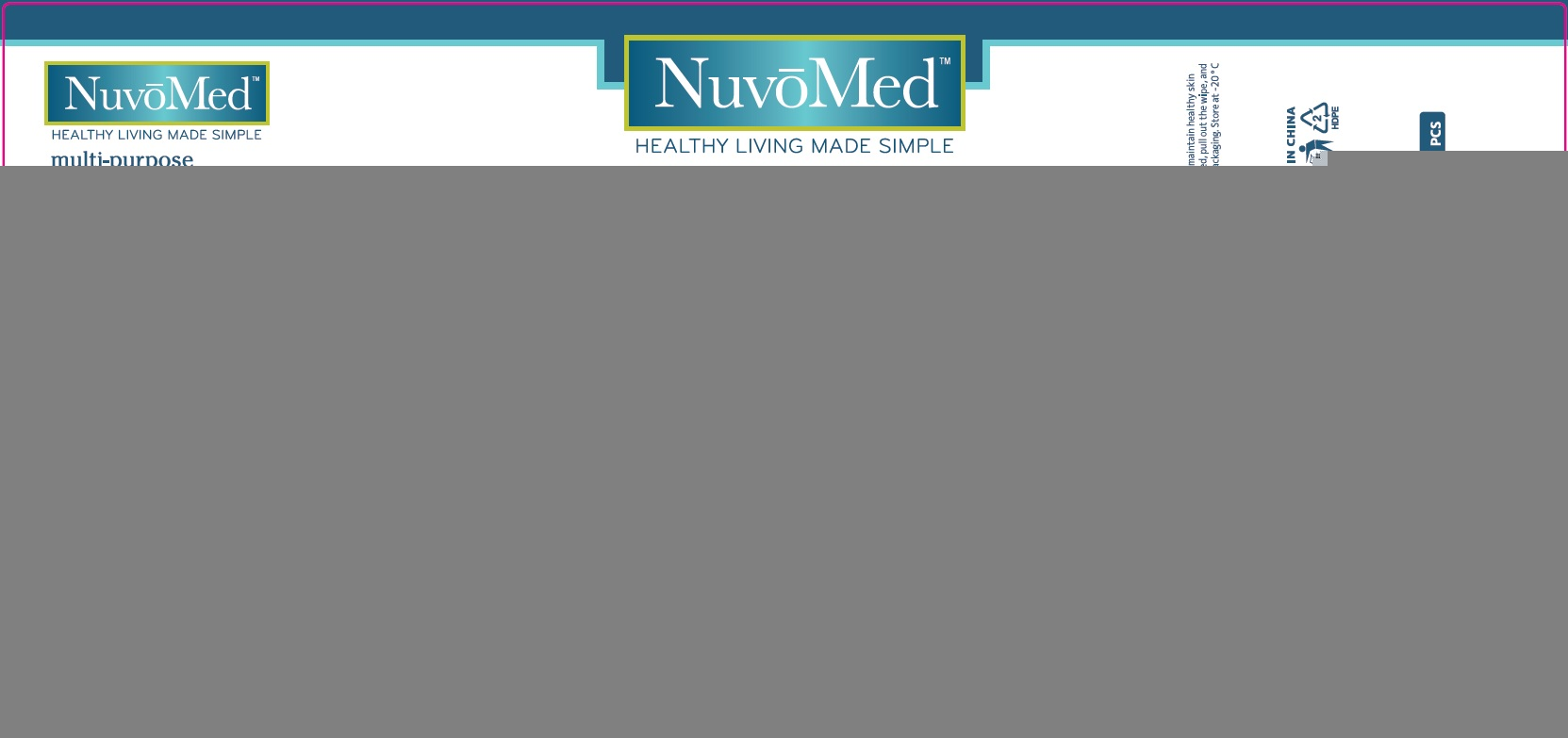 DRUG LABEL: NuvoMed Antibacterial Wet Wipes
NDC: 77435-004 | Form: SWAB
Manufacturer: HAINING LILY CLEANING PRODUCTS CO., LTD
Category: otc | Type: HUMAN OTC DRUG LABEL
Date: 20200528

ACTIVE INGREDIENTS: BENZALKONIUM CHLORIDE 0.3 g/100 g
INACTIVE INGREDIENTS: water; PROPYLENE GLYCOL; DIDECYLDIMONIUM CHLORIDE; phenoxyethanol; CHLORPHENESIN

Antibacterial Wipes

Active Ingredient

Benzalkonium Chloride 0.3%

Purpose

Antiseptic

USE

- For hand -washing to decrease bacteria on the skin when water is not available

Warning

- Flammable, keep away from fire or flame.
- For external use only.

When using this product

- do not get in eyes
- do ot use on open or broken skin
- if contact occurs, rinse eyes thoroughly with water

Stop use and ask a doctor

- if irritation and redness develops.

Other Information：

- Do not store above -20℃ to 30℃, away from sunlight

KEEP OUT OF REACH OF CHILDREN

If swallowed, get medical help or contact Poison Control Center right away

Directions

- Wet hands thoroughly with product and allow to dry 20-30 seconds, do not dry or wipe when finished

Inactive ingredients

Water, Propylene Glycol, Didecyldimonium Chloride, Phenoxyethanol, Chlorphenesin